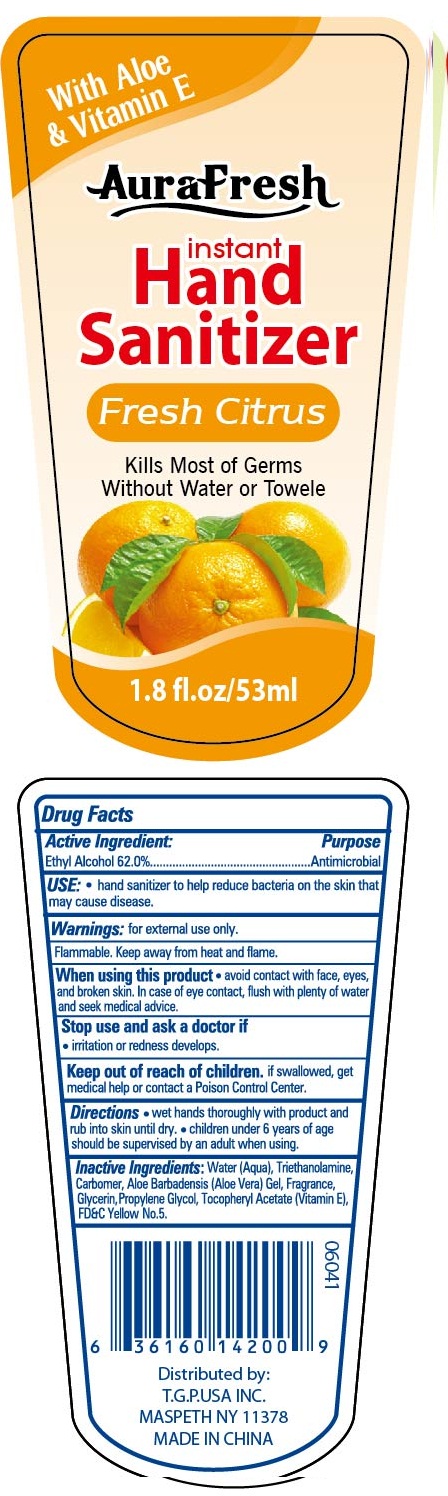 DRUG LABEL: aurafresh instant hand sanitizer with aloe and vitamin e
NDC: 40104-285 | Form: GEL
Manufacturer: Ningbo Pulisi Daily Chemical Products Co., Ltd.
Category: otc | Type: HUMAN OTC DRUG LABEL
Date: 20170810

ACTIVE INGREDIENTS: alcohol 62 mL/100 mL
INACTIVE INGREDIENTS: WATER; PROPYLENE GLYCOL; ALOE VERA LEAF; CARBOMER 934; GLYCERIN; .ALPHA.-TOCOPHEROL ACETATE; FD&C YELLOW NO. 5; TROLAMINE

Drug facts

Active ingredient Purpose

Ethyl Alcohol 62% ... Antiseptic

PURPOSE

Hand sanitizer to help reduce bacteria on the skin that may cause disease

KEEP OUT OF REACH OF CHILDREN

If swallowed, get medical help or contact local poison control center right away.

Children under 6 years of age shoud be supervised by an adult when using.

when using this product, avoid contact with face, eyes and broken skin. In case of eye contact, flush with plenty of water and seek medical advice.

WARNINGS

For external use only.
Flammable. Keep away from hear or flame.

Stop using and ask a doctor, if irritation and redness develops.

DOSAGE AND ADMINISTRATION

wet hands thoroughly with product and rub into skin until dry.

INACTIVE INGREDIENT

Water, Carbomer, Glycerin, Propylene Glycol, Triethanolamine, Aloe Barbadensis Leaf gel, Tocopheryl Acetate, Fragrance, yellow 5